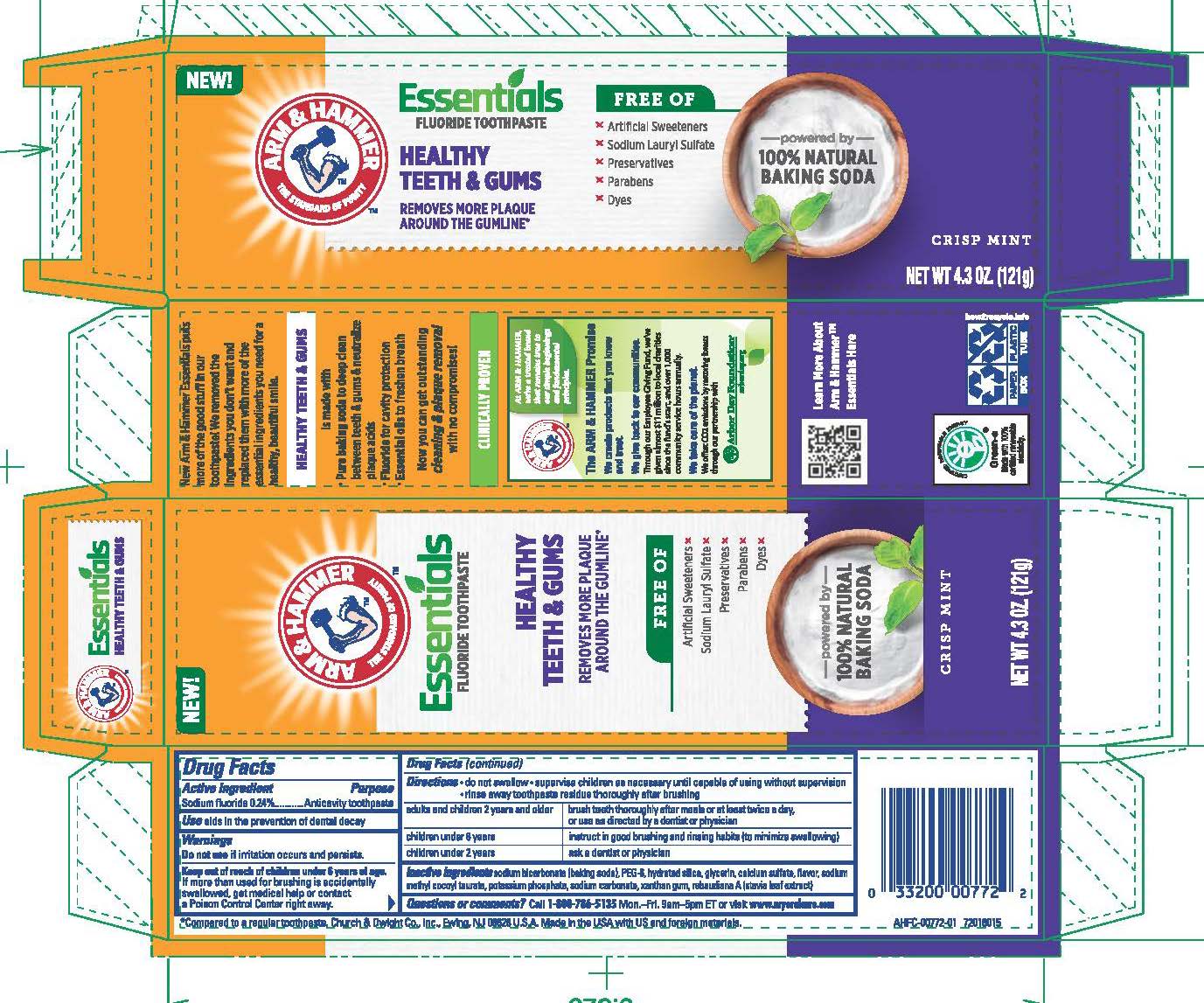 DRUG LABEL: Essentials Healthy Teeth and Gums
NDC: 10237-670 | Form: PASTE, DENTIFRICE
Manufacturer: Church & Dwight Co., Inc.
Category: otc | Type: HUMAN OTC DRUG LABEL
Date: 20250909

ACTIVE INGREDIENTS: SODIUM FLUORIDE 2.4 mg/1 g
INACTIVE INGREDIENTS: CALCIUM SULFATE; SODIUM BICARBONATE; SODIUM METHYL COCOYL TAURATE; POTASSIUM PHOSPHATE, UNSPECIFIED FORM; SODIUM CARBONATE; XANTHAN GUM; STEVIA REBAUDIANA WHOLE; POLYETHYLENE GLYCOL 400; HYDRATED SILICA; GLYCERIN; METHYL SALICYLATE

Arm and Hammer Essentials Healthy Teeth and Gums

ACTIVE INGREDIENT

Sodium fluoride 0.24%

PURPOSE

Anticavity toothpaste

INDICATIONS AND USAGE

Use aids in the prevention of dental decay

Do not use if irritation occurs and persists.

Keep out of reach of children under 6 years of age.
If more than used for brushing is accidentally swallowed, get medical help or contact a Poison Control Center right away.

Directions

- do not swallow
- supervise children as necessary until capable of using without supervision
- rinse away toothpaste residue thoroughly after brushing

adults and children 2 years and older - brush teeth thoroughly after meals or at least twice a day, or use as directed by a dentist or physician

children under 6 years - instruct in good brushing and rinsing habits (to minimize swallowing)

children under 2 years - ask a dentist or physician

INACTIVE INGREDIENT

sodium bicarbonate (baking soda), PEG-8, hydrated silica, glycerin, calcium sulfate, flavor, sodium methyl cocoyl taurate, potassium phosphate, sodium carbonate, xanthan gum, rebaudiana A (stevia leaf extract)

Questions or comments? Call 1-800-786-5135 Mon.-Fri. 9am-5pmET or visit www.myoralcare.com

PACKAGE LABEL

NEW!

ARM AND HAMMER

THE STANDARD OF PURITY

Essentials

FLUORIDE TOOTHPASTE

HEALTHY TEETH AND GUMS

REMOVES MORE PLAQUE

AROUND THE GUMLINE

FREE OF

Artificial Sweeteners

Sodium Lauryl Sulfate

Preservatives

Parabens

Dyes

powered by

100% NATURAL

BAKING SODA

CRISP MINT

NET WT 4.3 OZ. (121g)